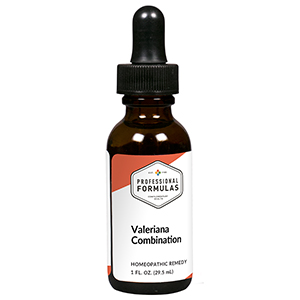 DRUG LABEL: Valeriana Combination
NDC: 63083-9249 | Form: LIQUID
Manufacturer: Professional Complementary Health Formulas
Category: homeopathic | Type: HUMAN OTC DRUG LABEL
Date: 20190815

ACTIVE INGREDIENTS: AVENA SATIVA FLOWERING TOP 1 [hp_X]/29.5 mL; ARTEMISIA ANNUA FLOWERING TOP 1 [hp_X]/29.5 mL; HAWTHORN LEAF WITH FLOWER 1 [hp_X]/29.5 mL; HOPS 1 [hp_X]/29.5 mL; VALERIAN 1 [hp_X]/29.5 mL; AMMONIUM BROMIDE 2 [hp_X]/29.5 mL; HEDEOMA PULEGIOIDES WHOLE 3 [hp_X]/29.5 mL; HYPERICUM PERFORATUM WHOLE 3 [hp_X]/29.5 mL; POTASSIUM BROMIDE 3 [hp_X]/29.5 mL; SODIUM BROMIDE 3 [hp_X]/29.5 mL; PICRIC ACID 6 [hp_X]/29.5 mL
INACTIVE INGREDIENTS: ALCOHOL; WATER

R249

ACTIVE INGREDIENTS

Avena sativa 1X
Chamomilla 1X
Crataegus oxyacantha 1X
Humulus lupulus 1X
Valeriana officinalis 1X
Ammonium bromatum 2X
Hedeoma pulegioides 3X
Hypericum perforatum 3X
Kali bromatum 3X
Natrum bromatum 3X
Picricum acidum 6X

QUESTIONS

Professional Formulas

PO Box 2034 Lake Oswego, OR 97035

INDICATIONS

For the temporary relief of insomnia, restlessness, or work-related stress.*

PURPOSE

*Claims based on traditional homeopathic practice, not accepted medical evidence. Not FDA evaluated.

WARNINGS

In case of overdose, get medical help or contact a poison control center right away.

Keep out of the reach of children.

PREGNANCY OR BREAST FEEDING

If pregnant or breastfeeding, ask a healthcare professional before use.

DIRECTIONS

Place drops under tongue 30 minutes before/after meals. Adults and children 12 years and over: Take 10 drops up to 3 times per day. Consult a physician for use in children under 12 years of age.

OTHER INFORMATION

Tamper resistant. If seal is broken, do not use. After opening, close container tightly and store at room temperature away from heat.

INACTIVE INGREDIENTS

40% ethanol, purified water.

LABEL

Est 1985

Professional Formulas

Complementary Health

Valeriana Combination

Homeopathic Remedy

1 FL. OZ. (29.5 mL)